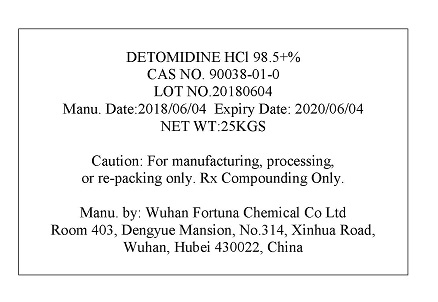 DRUG LABEL: Detomidine Hydrochloride
NDC: 27816-0665 | Form: POWDER
Manufacturer: Wuhan Fortuna Chemical Co Ltd
Category: other | Type: BULK INGREDIENT
Date: 20181119

ACTIVE INGREDIENTS: DETOMIDINE HYDROCHLORIDE 1 kg/1 kg

PACKAGE LABEL

Detomidine_HCl_label.jpg